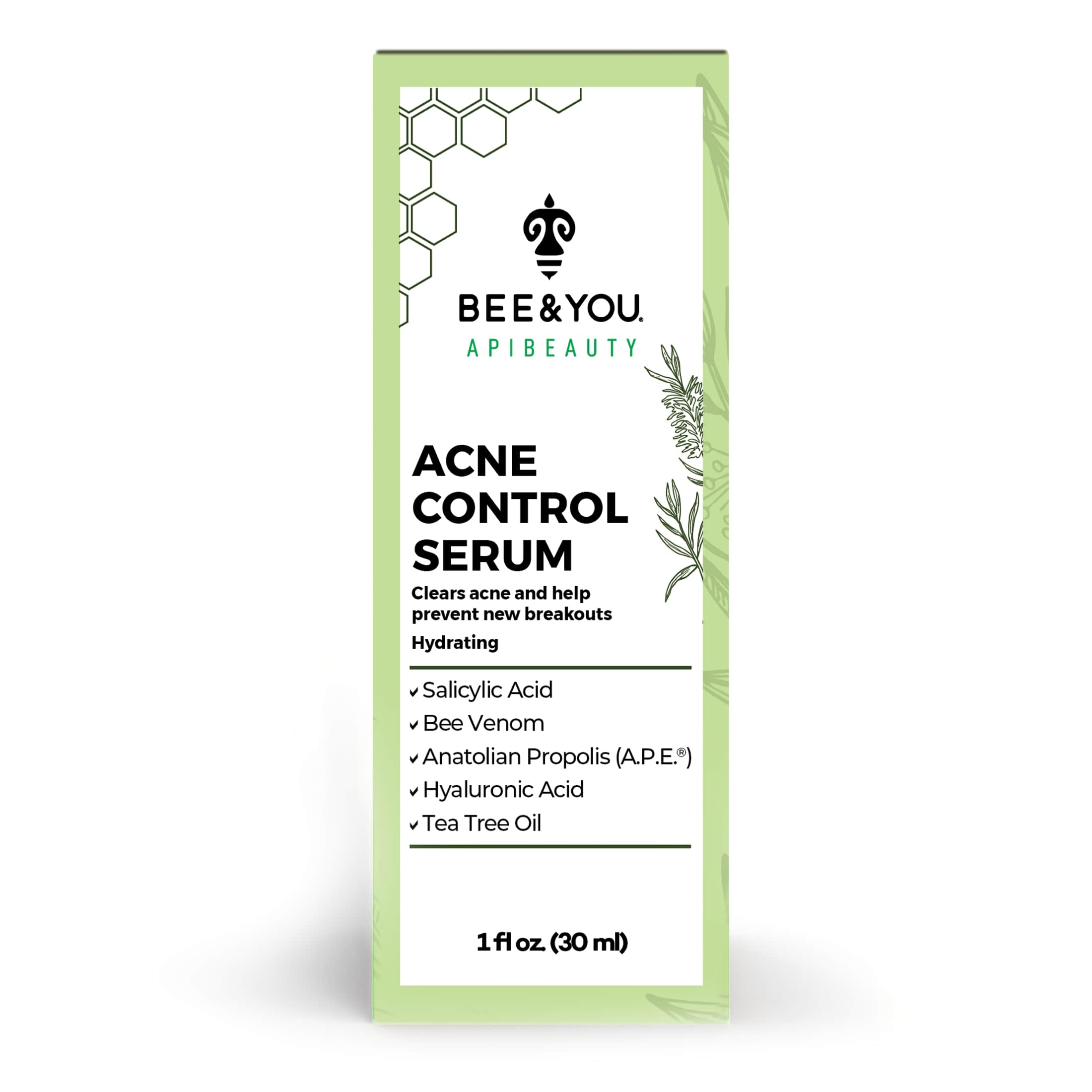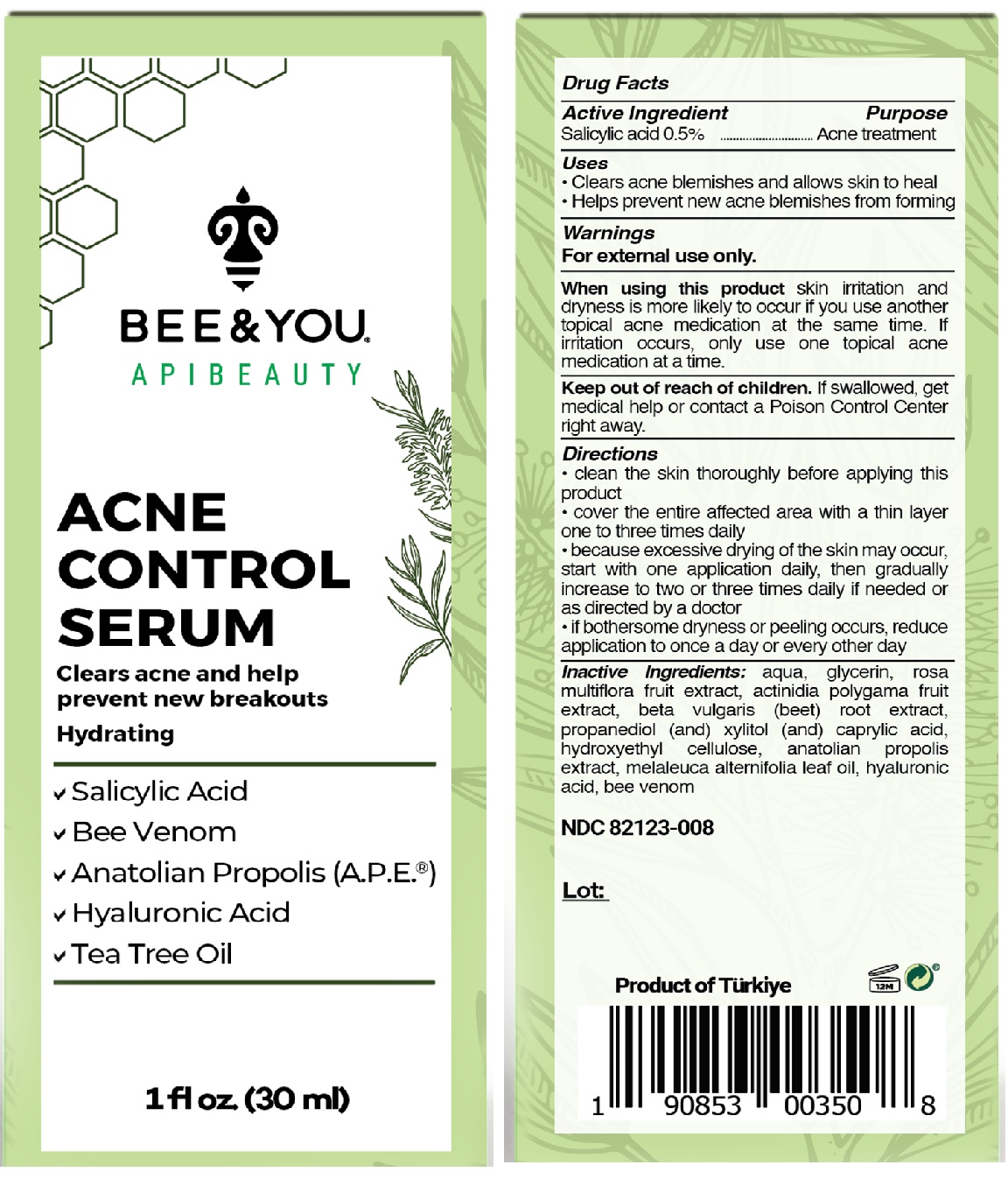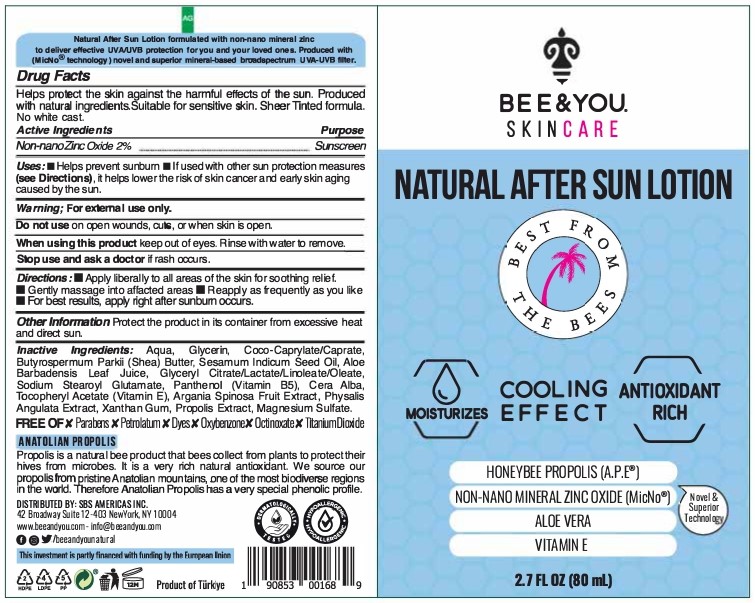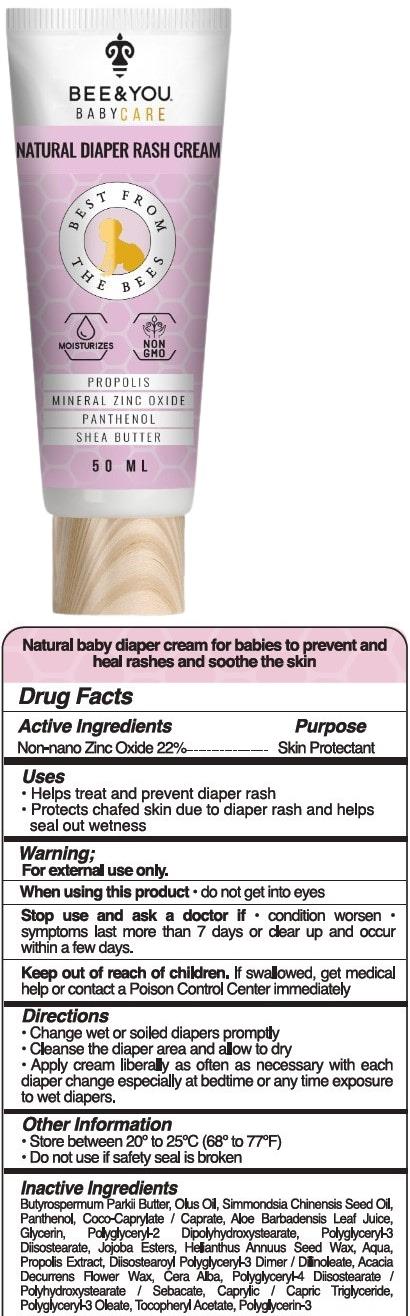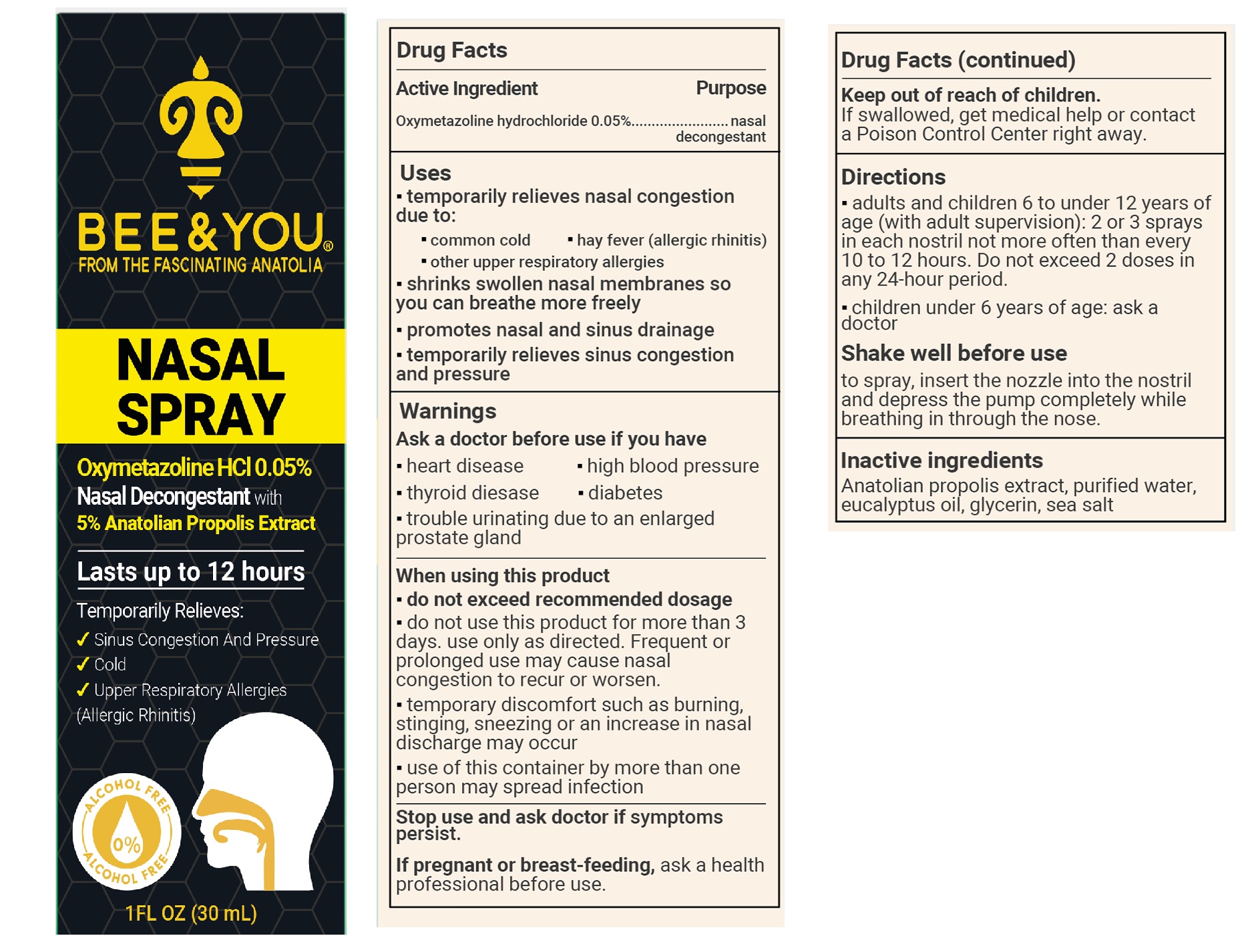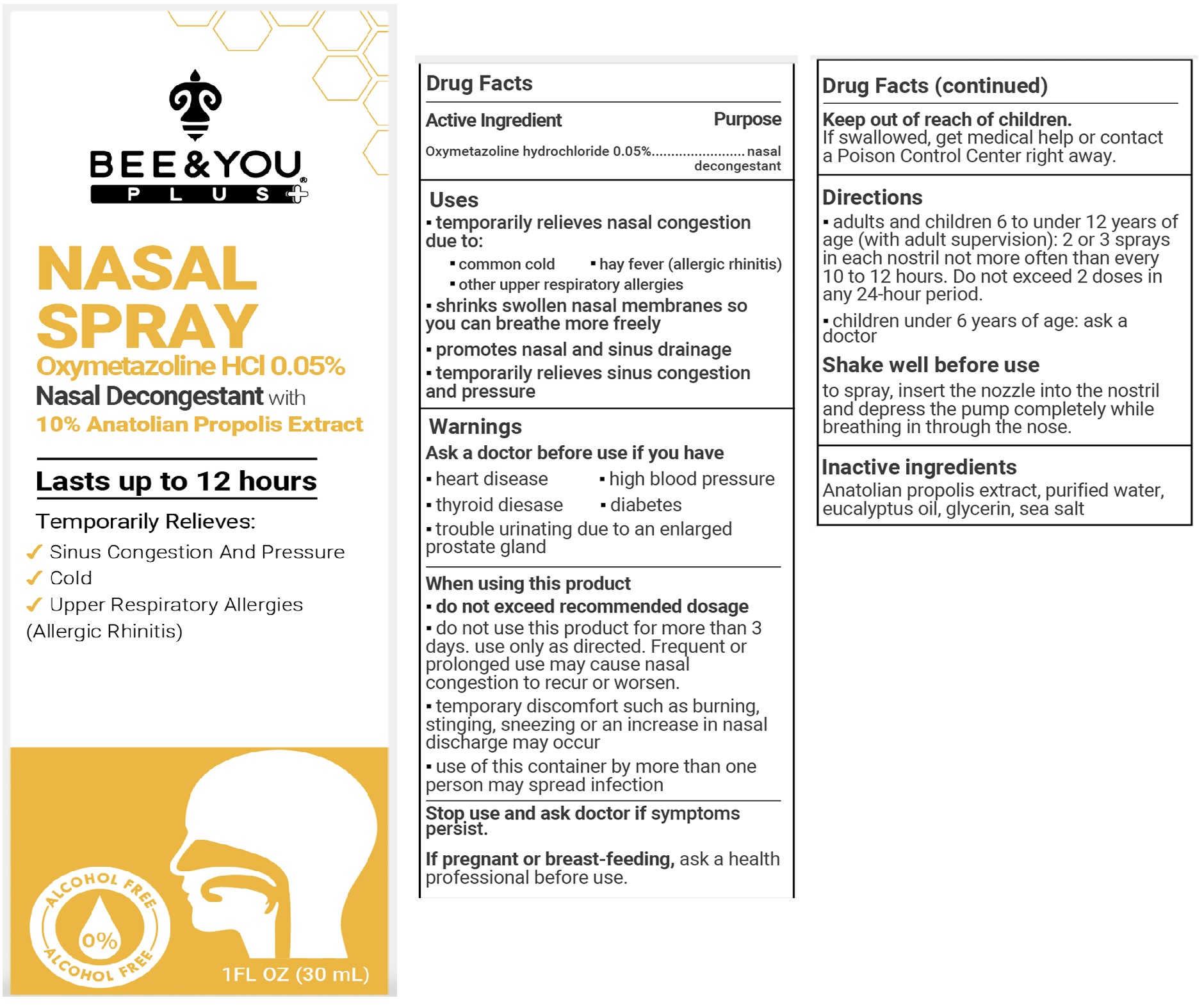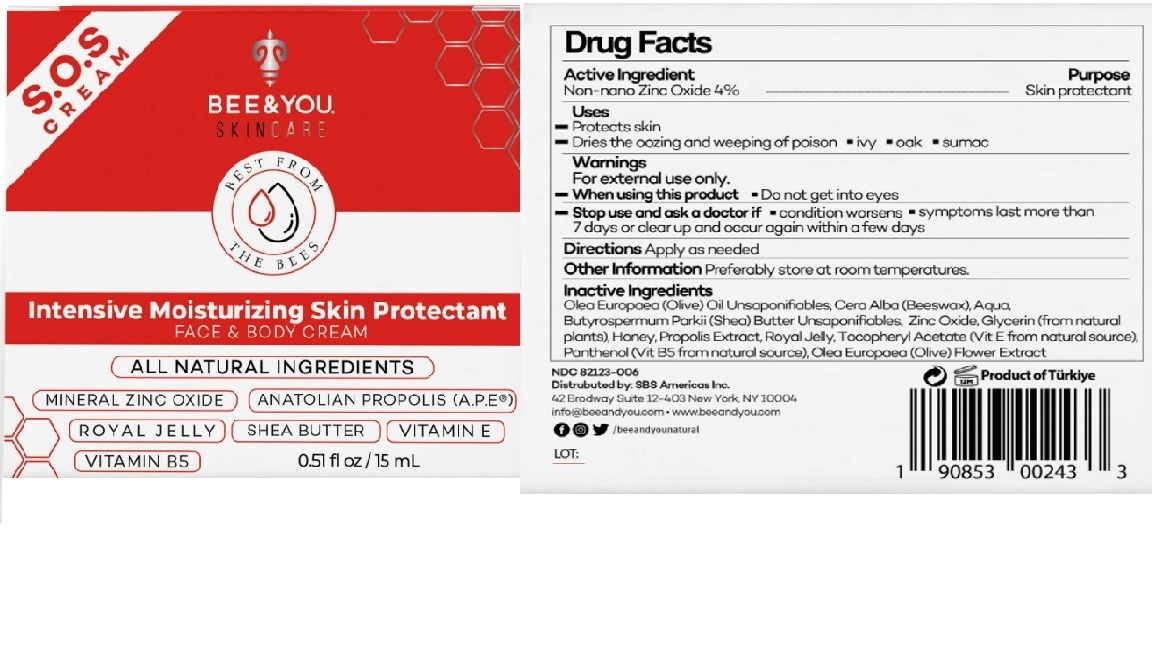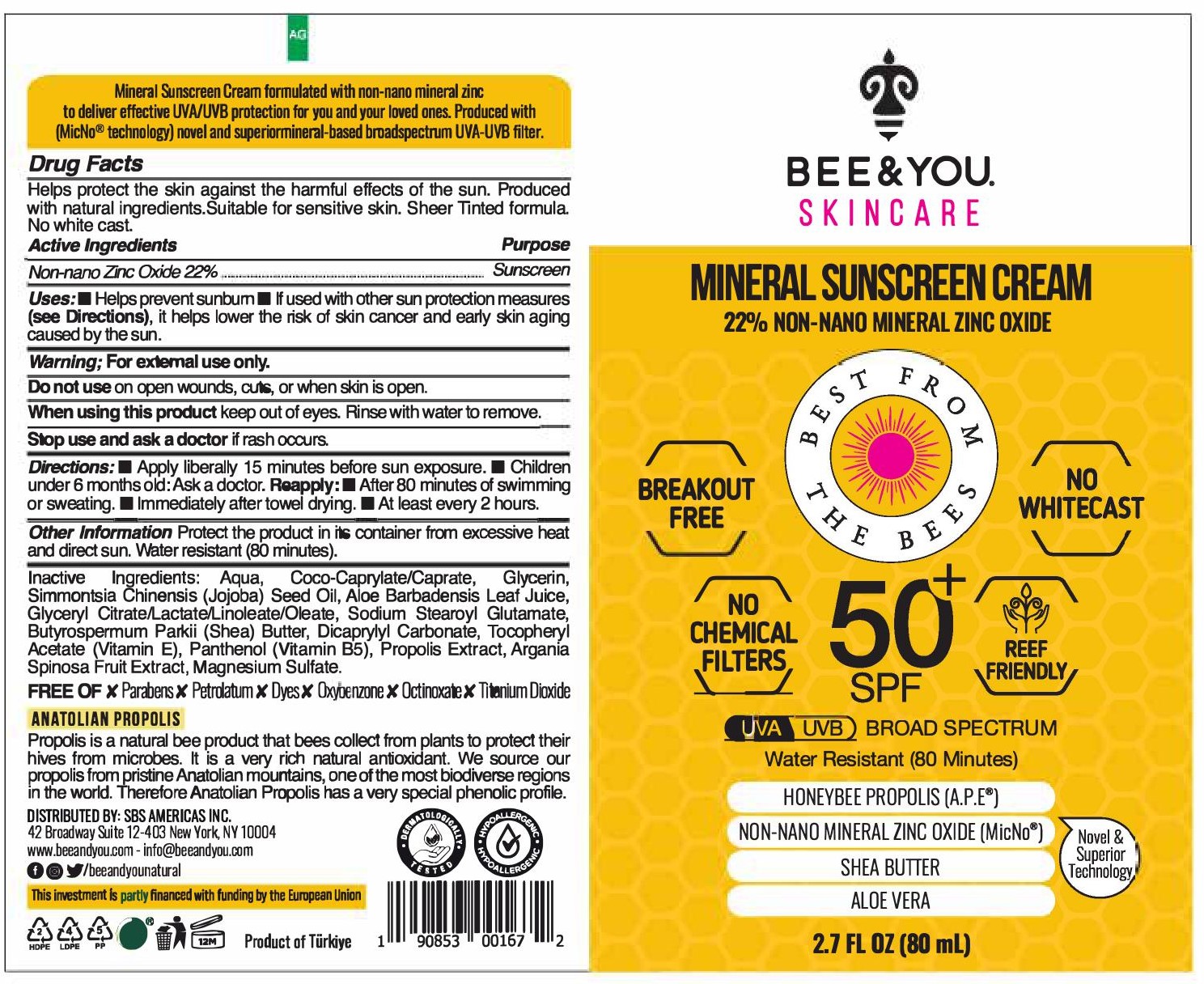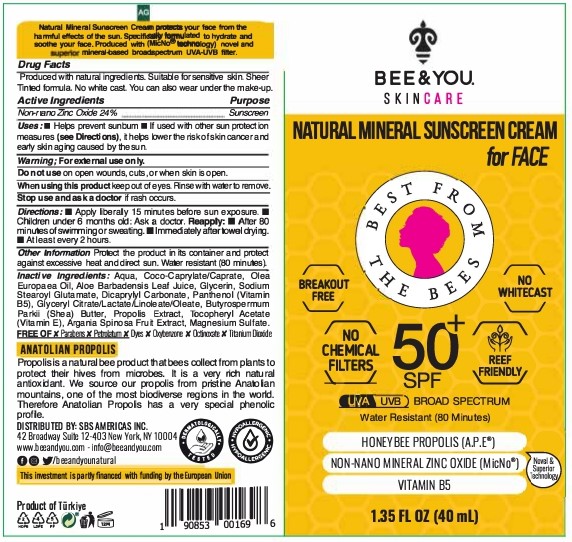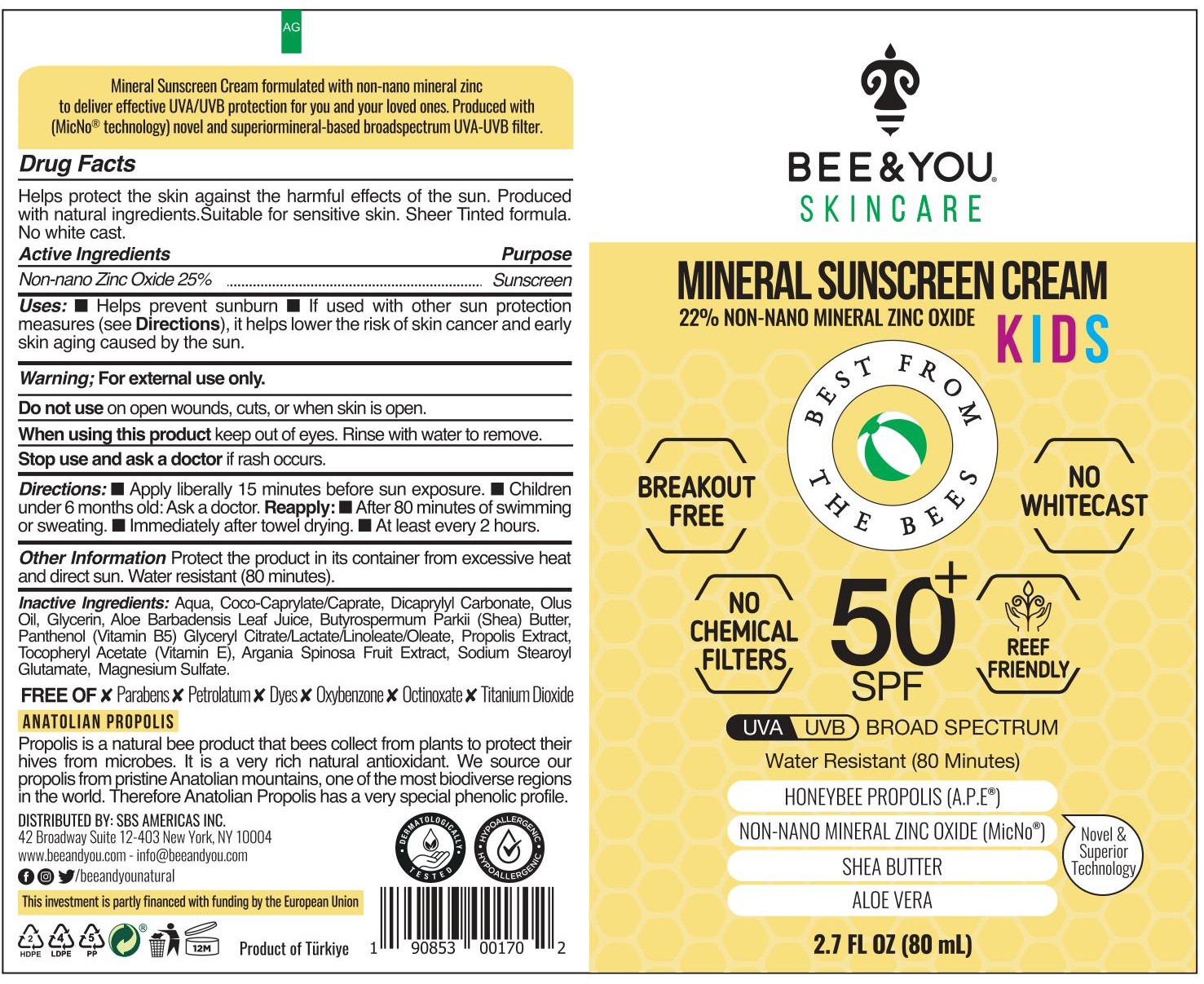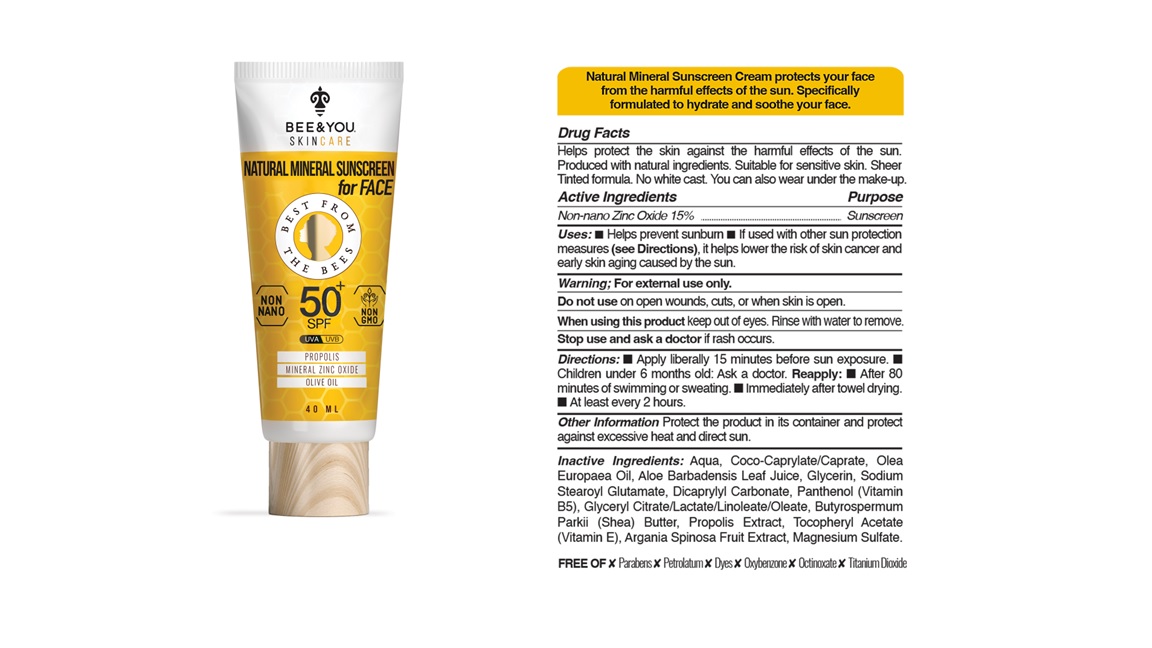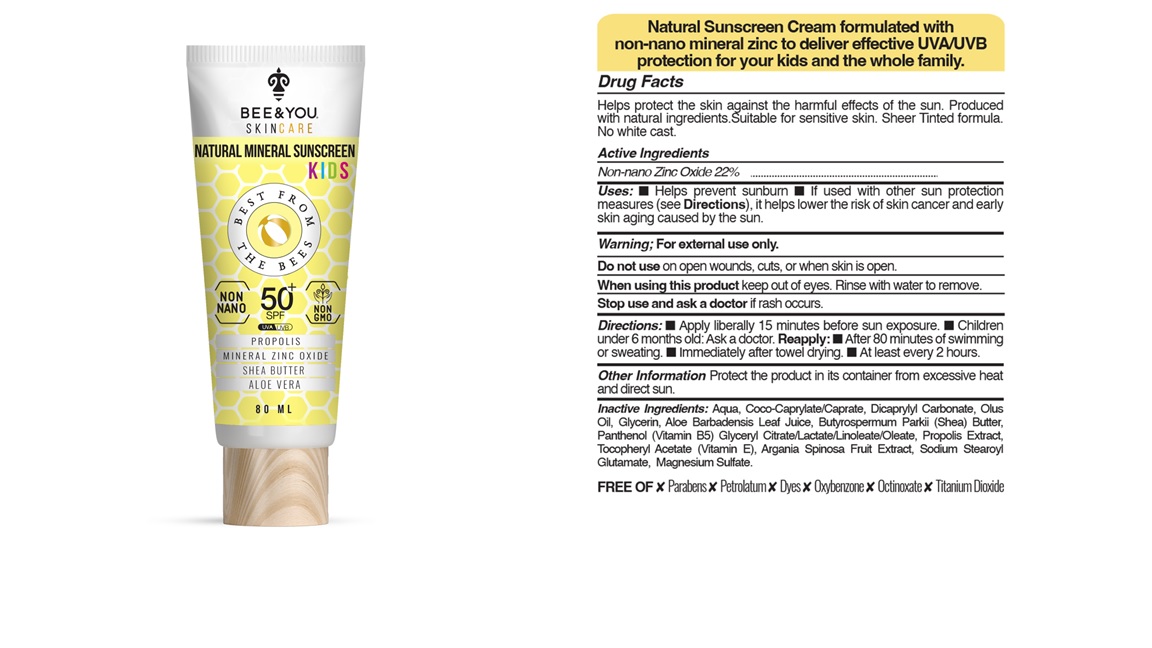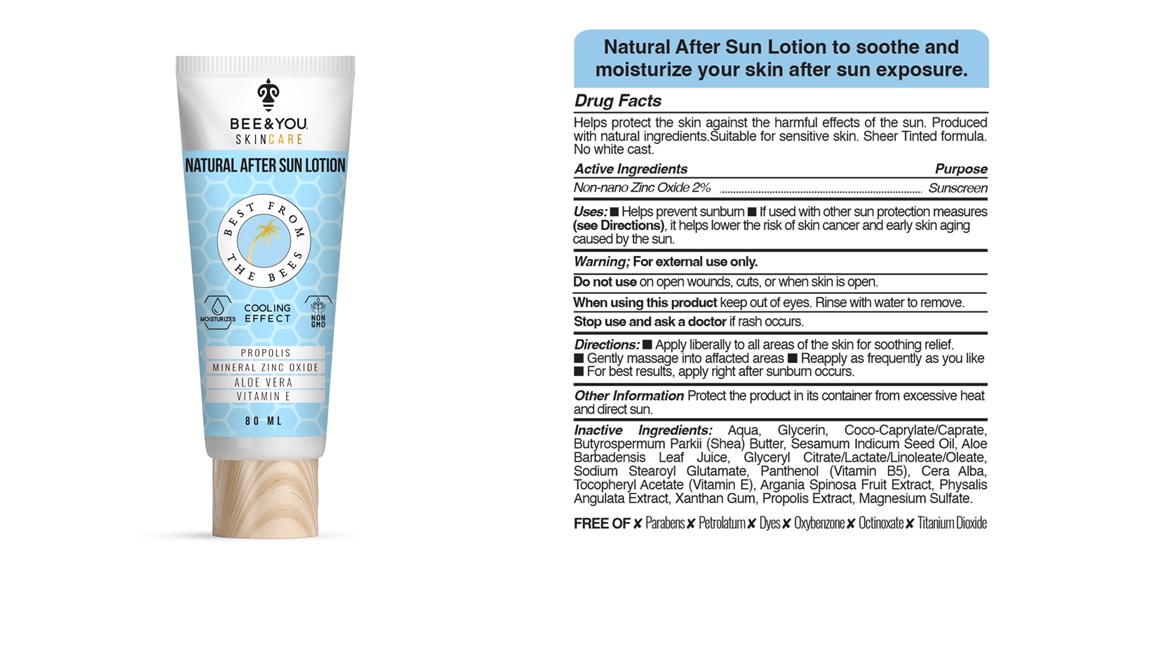 DRUG LABEL: PROPOLIS NASAL PLUS
NDC: 82123-021 | Form: LIQUID
Manufacturer: SBS BILIMSEL BIO COZUMLER SANAYI VE TICARET ANONIM SIRKETI PINAR SUBESI
Category: otc | Type: HUMAN OTC DRUG LABEL
Date: 20260127

ACTIVE INGREDIENTS: OXYMETAZOLINE HYDROCHLORIDE 15.21 mg/30 mL
INACTIVE INGREDIENTS: EUCALYPTUS OIL; WATER; SEA SALT; PROPOLIS WAX; GLYCERIN

Active Ingredient(s)

Alcohol 80% v/v. Purpose: Antiseptic

Purpose

Antiseptic, Hand Sanitizer

Use

Hand Sanitizer to help reduce bacteria that potentially can cause disease. For use when soap and water are not available.

Warnings

For external use only. Flammable. Keep away from heat or flame

Do not use

- in children less than 2 months of age
- on open skin wounds

When using this product keep out of eyes, ears, and mouth. In case of contact with eyes, rinse eyes thoroughly with water.
Stop use and ask a doctor if irritation or rash occurs. These may be signs of a serious condition.
Keep out of reach of children. If swallowed, get medical help or contact a Poison Control Center right away.

Stop use and ask a doctor if irritation or rash occurs. These may be signs of a serious condition.

Keep out of reach of children. If swallowed, get medical help or contact a Poison Control Center right away.

Directions

- Place enough product on hands to cover all surfaces. Rub hands together until dry.
- Supervise children under 6 years of age when using this product to avoid swallowing.

Other information

- Store between 15-30C (59-86F)
- Avoid freezing and excessive heat above 40C (104F)

Acne Control Serum

30 ml NDC: 82123-009

Diaper Rash Cream

Diaper Rash Cream50 mL NDC: 82123-005

SOS Cream